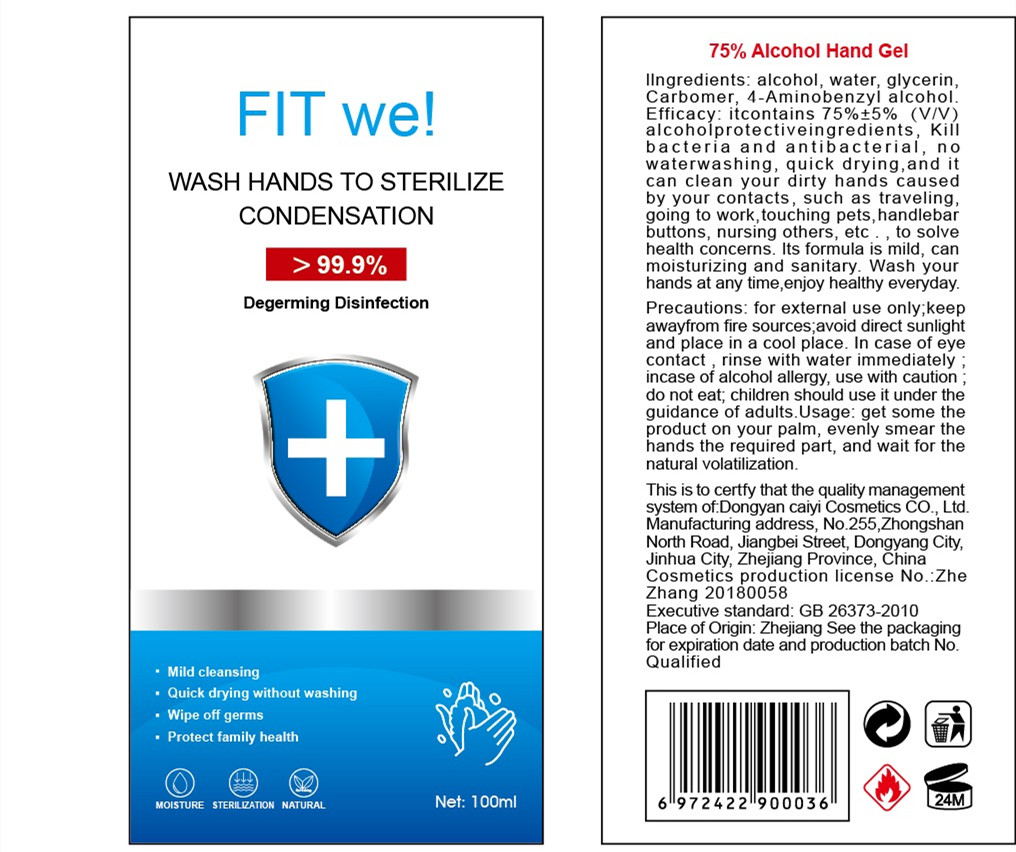 DRUG LABEL: Hand sanitizer
NDC: 54096-001 | Form: GEL
Manufacturer: Dongyang Caiyi Cosmetics Co., Ltd.
Category: otc | Type: HUMAN OTC DRUG LABEL
Date: 20200423

ACTIVE INGREDIENTS: ALCOHOL 75 mL/100 mL
INACTIVE INGREDIENTS: WATER; CARBOMER HOMOPOLYMER, UNSPECIFIED TYPE; M-AMINOBENZYL ALCOHOL; GLYCERIN

DOSAGE AND ADMINISTRATION

keep away from fire sources;avoid direct sunlight

INACTIVE INGREDIENT

AQUA、GLYCERIN、CARBOMER、4- AMINOBENZYL ALCOHOL

INDICATIONS AND USAGE

get some the product on your palm, evenly smear the hands the required part, and wait for the natural volatilization.

ACTIVE INGREDIENT

ALCOHOL

keep out of children

PURPOSE

Mild cleansing
Quick drying without washing
Wipe off germs
Protect family health

WARNINGS

for external use only;keep awayfrom fire sources;avoid direct sunlight vand place in a cool place. In case of eye contact，rinse with water immediately ;incase of alcohol allergy, use with caution ;do not eat; children should use it under the guidance of adults.